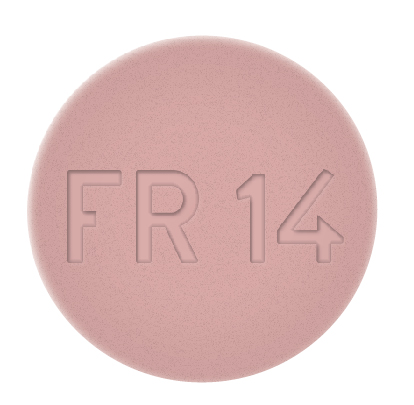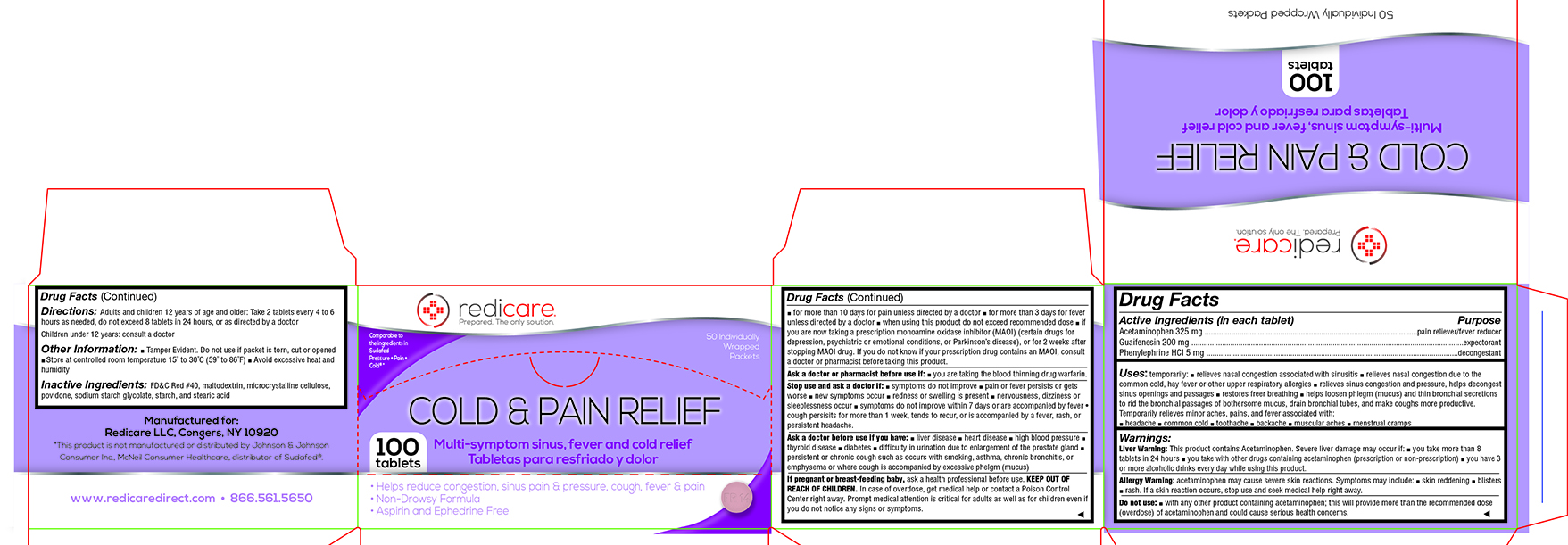 DRUG LABEL: Cold and Sinus Pain Relief
NDC: 71105-106 | Form: TABLET
Manufacturer: Redicare LLC
Category: otc | Type: HUMAN OTC DRUG LABEL
Date: 20210702

ACTIVE INGREDIENTS: PHENYLEPHRINE HYDROCHLORIDE 5 mg/1 1; GUAIFENESIN 200 mg/1 1; ACETAMINOPHEN 325 mg/1 1
INACTIVE INGREDIENTS: FD&C RED NO. 40; SODIUM STARCH GLYCOLATE TYPE A CORN; STEARIC ACID; CELLULOSE, MICROCRYSTALLINE; POVIDONE; STARCH, CORN

Cold Tabs

Active Ingredients (in each tablet) .........................................Purpose

Acetaminophen 325 mg ........................................................................................................pain reliever/fever reducer

Guaifenesin 200 mg .....................................................................................................................................expectorant

Phenylephrine HCI 5 mg ...........................................................................................................................decongestant

Uses:

temporarily: ■ relieves nasal congestion associated with sinusitis ■ relieves nasal congestion due to the common cold, hay fever or other upper respiratory allergies ■ relieves sinus congestion and pressure, helps decongest sinus openings and passages ■ restores freer breathing ■ helps loosen phlegm (mucus) and thin bronchial secretions to rid the bronchial passages of bothersome mucus, drain bronchial tubes, and make coughs more productive. Temporarily relieves minor aches, pains, and fever associated with: ■ headache ■ common cold ■ toothache ■ backache ■ muscular aches ■ menstrual cramps

Liver Warning:

This product contains Acetaminophen. Severe liver damage may occur if: ■ you take more than 8 tablets in 24 hours ■ you take with other drugs containing acetaminophen (prescription or non-prescription) ■ you have 3 or more alcoholic drinks every day while using this product.

Allergy Warning:

acetaminophen may cause severe skin reactions. Symptoms may include: ■ skin reddening ■ blisters ■ rash. If a skin reaction occurs, stop use and seek medical help right away.

Do not use:

■ with any other product containing acetaminophen; this will provide more than the recommended dose (overdose) of acetaminophen and could cause serious health concerns. ■ for more than 10 days for pain unless directed by a doctor ■ for more than 3 days for fever unless directed by a doctor ■ when using this product do not exceed recommended dose ■ if you are now taking a prescription monoamine oxidase inhibitor (MAOI) (certain drugs for depression, psychiatric or emotional conditions, or Parkinson’s disease), or for 2 weeks after stopping MAOI drug. If you do not know if your prescription drug contains an MAOI, consult a doctor or pharmacist before taking this product.

Ask a doctor or pharmacist before use if:

■ you are taking the blood thinning drug warfarin.

Stop use and ask a doctor if:

■ symptoms do not improve ■ pain or fever persists or gets worse ■ new symptoms occur ■ redness or swelling is present ■ nervousness, dizziness or sleeplessness occur ■ symptoms do not improve within 7 days or are accompanied by a fever • cough persists for more than 1 week, tends to recur, or is accompanied by a fever, rash, or persistent headache.

Ask a doctor before use if you have:

■ liver disease ■ heart disease ■ high blood pressure ■ thyroid disease ■ diabetes ■ difficulty in urination due to enlargement of the prostate gland ■ persistent or chronic cough such as occurs with smoking, asthma, chronic bronchitis, or emphysema or where cough is accompanied by excessive phlegm (mucus)

If pregnant or breast-feeding baby,

ask a health professional before use.

KEEP OUT OF REACH OF CHILDREN.

In case of overdose, get medical help or contact a Poison Control Center right away. Prompt medical attention is critical for adults as well as for children even if you do not notice any signs or symptoms.

Directions:

Adults and children 12 years of age and older: Take 2 tablets every 4 to 6 hours as needed, do not exceed 8 tablets in 24 hours, or as directed by a doctor.
Children under 12 years: consult a doctor

Other Information

■ Tamper Evident. Do not use if packet is torn, cut or opened ■ Store at controlled room temperature 15˚ to 30˚C (59˚ to 86˚F) ■ Avoid excessive heat and humidity

Inactive Ingredients:

FD&C Red #40, maltodextrin, microcrystalline cellulose, povidone, sodium starch glycolate, starch, and stearic acid